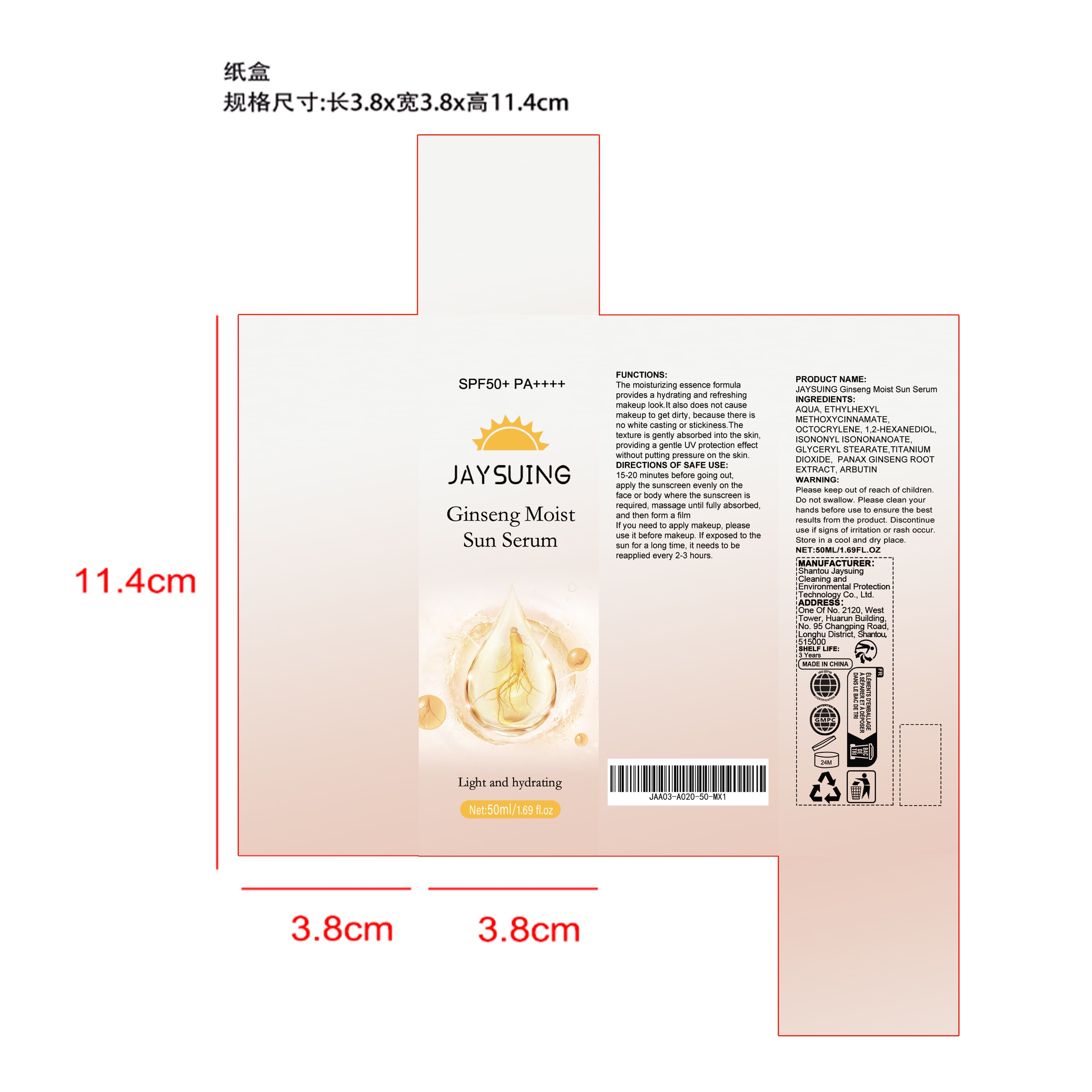 DRUG LABEL: JAYSUING Ginseng Moist Sun Serum
NDC: 85060-011 | Form: LIQUID
Manufacturer: Shantou Jaysuing Cleaning and Environmental Protection Technology Co., Ltd.
Category: otc | Type: HUMAN OTC DRUG LABEL
Date: 20251208

ACTIVE INGREDIENTS: PANAX GINSENG ROOT OIL 0.005 mg/50 mg
INACTIVE INGREDIENTS: ETHYLHEXYL METHOXYCINNAMATE 3 mg/50 mg; TITANIUM DIOXIDE 0.5 mg/50 mg; AQUA 40.59 mg/50 mg; OCTOCRYLENE 3 mg/50 mg; ISONONYL ISONONANOATE 2 mg/50 mg; ARBUTIN 0.005 mg/50 mg; GLYCERYL STEARATE 0.75 mg/50 mg; 1,2-HEXANEDIOL 0.15 mg/50 mg

ACTIVE INGREDIENT

PANAX GINSENG ROOT EXTRACT

PURPOSE

The moisturizing essence formula provides a hydrating and refreshing makeup look. It also does not cause makeup to get dirty, because there is no white casting or stickiness. The texture is gently absorbed into the skin, providing a gentle UV protection effect without putting pressure on the skin.

WHEN USING

15-20 minutes before going out,apply the sunscreen evenly on the face or body where the sunscreen is required, massage until fully absorbed, and then form a film.If you need to apply makeup, please use it before makeup. If exposed to the sun for a long time, it needs to be reapplied every 2-3 hours.

WARNINGS

Please keep out of reach of children. Do not swallow.Please clean your hands before use to ensure the best results from the product. Discontinue use if signs of irritation or rash occur. Store in a cool and dry place.

DO NOT USE

Discontinue use if signs of irritation or rash occur.

STOP USE

Discontinue use if signs of irritation or rash occur.

KEEP OUT OF REACH OF CHILDREN

Please keep out of reach of children. Do not swallow.

STORAGE AND HANDLING

Store in a cool and dry place.

INACTIVE INGREDIENT

AQUA、ETHYLHEXYL METHOXYCINNAMATE、

OCTOCRYLENE、1,2-HEXANEDIOL、ISONONYL ISONONANOATE、

GLYCERYL STEARATE、TITANIUM DIOXIDE、ARBUTIN

DOSAGE AND ADMINISTRATION

15-20 minutes before going out,apply the sunscreen evenly on the face or body where the sunscreen is required, massage until fully absorbed, and then form a film.If you need to apply makeup, please use it before makeup. If exposed to the sun for a long time, it needs to be reapplied every 2-3 hours.

INDICATIONS AND USAGE

15-20 minutes before going out,apply the sunscreen evenly on the face or body where the sunscreen is required, massage until fully absorbed, and then form a film.If you need to apply makeup, please use it before makeup. If exposed to the sun for a long time, it needs to be reapplied every 2-3 hours.